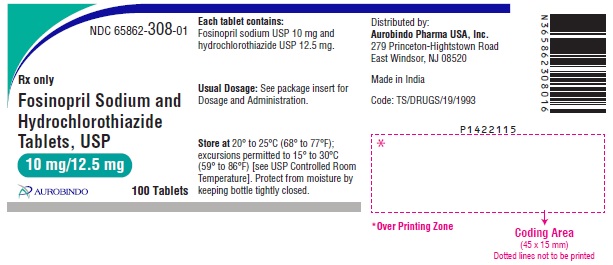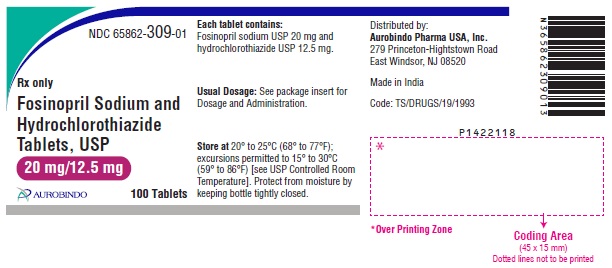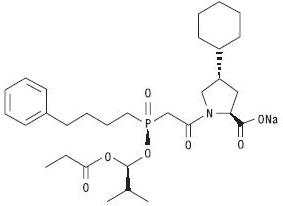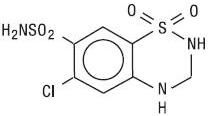 DRUG LABEL: Fosinopril Sodium and Hydrochlorothiazide
NDC: 65862-308 | Form: TABLET
Manufacturer: Aurobindo Pharma Limited
Category: prescription | Type: Human Prescription Drug Label
Date: 20240428

ACTIVE INGREDIENTS: FOSINOPRIL SODIUM 10 mg/1 1; HYDROCHLOROTHIAZIDE 12.5 mg/1 1
INACTIVE INGREDIENTS: ANHYDROUS LACTOSE; FERRIC OXIDE RED; FERRIC OXIDE YELLOW; CROSCARMELLOSE SODIUM; POVIDONE K30; ISOPROPYL ALCOHOL; GLYCERYL DISTEARATE; SODIUM LAURYL SULFATE

Fosinopril Sodium and Hydrochlorothiazide Tablets, USP
Rx only

WARNING: FETAL TOXICITY

- When pregnancy is detected, discontinue fosinopril and hydrochlorothiazide as soon as possible.
- Drugs that act directly on the renin-angiotensin system can cause injury and death to the developing fetus. See WARNINGS: Fetal Toxicity

DESCRIPTION

Fosinopril sodium, USP is a white to almost white powder, soluble (>100 mg/mL) in water, in ethanol, and in methanol, and slightly soluble in hexane. Fosinopril sodium is designated chemically as L-proline, 4-cyclohexyl-1-[[[2-methyl-1-(1-oxopropoxy)propoxy](4-phenylbutyl)phosphinyl]acetyl]-, sodium salt, trans-; its structural formula is:

Its molecular formula is C30H45NNaO7P, and its molecular weight is 585.65.

Fosinoprilat, the active metabolite of fosinopril, is a non-sulfhydryl angiotensin-converting enzyme inhibitor. Fosinopril is converted to fosinoprilat by hepatic cleavage of the ester group.

Hydrochlorothiazide, USP is a white or practically white, practically odorless, crystalline powder. It is slightly soluble in water; freely soluble in sodium hydroxide solution, in n-butylamine, and in dimethylformamide; sparingly soluble in methanol; and insoluble in ether, in chloroform, and in dilute mineral acids. Hydrochlorothiazide is designated chemically as 6-chloro-3,4-dihydro-2H-1,2,4-benzothiadiazine-7-sulfonamide 1,1-dioxide; its structural formula is:

Its molecular formula is C7H8ClN3O4S2, and its molecular weight is 297.73. Hydrochlorothiazide is a thiazide diuretic.

Fosinopril sodium and hydrochlorothiazide tablets, USP are a combination of fosinopril sodium, USP and hydrochlorothiazide, USP. They are available for oral use in two tablet strengths: fosinopril sodium and hydrochlorothiazide tablets, USP 10 mg/12.5 mg, containing 10 mg of fosinopril sodium, USP and 12.5 mg of hydrochlorothiazide, USP; and fosinopril sodium and hydrochlorothiazide tablets, USP 20 mg/12.5 mg, containing 20 mg of fosinopril sodium, USP and 12.5 mg of hydrochlorothiazide, USP. The inactive ingredients of the tablets include lactose anhydrous, ferric oxide red, ferric oxide yellow, croscarmellose sodium, povidone, isopropyl alcohol, glyceryl distearate, and sodium lauryl sulfate.

CLINICAL PHARMACOLOGY

Mechanism of Action

Fosinopril and fosinoprilat inhibit angiotensin-converting enzyme (ACE) in human subjects and in animals. ACE is a peptidyl dipeptidase that catalyzes the conversion of angiotensin I to the vasoconstrictor substance, angiotensin II. Angiotensin II also stimulates aldosterone secretion by the adrenal cortex. Inhibition of ACE results in decreased plasma angiotensin II, which leads to decreased vasopressor activity and to decreased aldosterone secretion. The latter decrease may result in a small increase of serum potassium. Hypertensive patients treated with fosinopril alone for an average of 8 weeks had elevations of serum potassium of approximately 0.1 mEq/L. Similar patients treated with hydrochlorothiazide alone had a mean reduction in serum potassium of 0.15 mEq/L, while patients who received combined treatment with 10/12.5 mg or 20/12.5 mg of fosinopril and hydrochlorothiazide had reductions of 0.07 and 0.03 mEq/L, respectively. (See PRECAUTIONS.)

Removal of angiotensin II negative feedback on renin secretion leads to increased plasma renin activity.

ACE is identical to kininase, an enzyme that degrades bradykinin. Whether increased levels of bradykinin, a potent vasodepressor peptide, play a role in the therapeutic effects of fosinopril sodium and hydrochlorothiazide tablets remains to be elucidated.

While the mechanism through which fosinopril lowers blood pressure is believed to be primarily suppression of the renin-angiotensin-aldosterone system, fosinopril has an antihypertensive effect even in patients with low-renin hypertension.

Hydrochlorothiazide is a thiazide diuretic. Thiazides affect the renal tubular mechanisms of electrolyte reabsorption, directly increasing excretion of sodium and chloride in approximately equivalent amounts. Indirectly, the diuretic action of hydrochlorothiazide reduces plasma volume, with consequent increases in plasma renin activity, increases in aldosterone secretion, increases in urinary potassium loss, and decreases in serum potassium. The renin-aldosterone link is mediated by angiotensin, so coadministration of an ACE inhibitor tends to reverse the potassium loss associated with these diuretics.

The mechanism of the antihypertensive effect of thiazides is unknown.

Pharmacokinetics and Metabolism

The absolute absorption of fosinopril averages 36% of an oral dose. The primary site of absorption is the proximal small intestine. While the rate of absorption may be slowed by the presence of food in the gastrointestinal tract, the extent of absorption of fosinopril is essentially unaffected.

Following oral administration of hydrochlorothiazide, peak plasma concentrations are achieved in 1 to 2.5 hours, and the extent of absorption is 50 to 80%. The reported studies of food effects on hydrochlorothiazide absorption have been inconclusive. The absorption of hydrochlorothiazide is increased by agents that reduce gastrointestinal motility. It is reported to be decreased by 50% in patients with congestive heart failure.

Cleavage of the ester group (primarily in the liver) converts fosinopril to its active metabolite, fosinoprilat. The time to peak plasma concentrations of fosinoprilat is about 3 hours, independent of the administered dose of fosinopril. In patients with hepatic dysfunction due to cirrhosis, conversion of fosinopril to fosinoprilat may be slowed, but the extent of this conversion is unchanged.

Fosinoprilat is highly protein bound (95%), but has negligible binding to cellular components of blood. The peak serum concentration and the area under the concentration-time curve of fosinoprilat is directly proportional to the administered dose of fosinopril.

After an oral dose of radiolabeled fosinopril, 75% of radioactivity in plasma was present as active fosinoprilat, 20 to 30% as a glucuronide conjugate of fosinoprilat, and 1 to 5% as a p-hydroxy metabolite of fosinoprilat. Since fosinoprilat is not biotransformed after intravenous administration, fosinopril, not fosinoprilat, appears to be the precursor for the glucuronide and p-hydroxy metabolites. In rats, the p-hydroxy metabolite of fosinoprilat is as potent an inhibitor of ACE as fosinoprilat; the glucuronide conjugate is devoid of ACE inhibitory activity.

Studies in animals indicate that fosinopril and fosinoprilat do not cross the blood-brain barrier, but fosinoprilat does cross the placenta of pregnant animals. In humans, hydrochlorothiazide crosses the placenta freely, and levels in umbilical-cord blood are similar to those in the maternal circulation.

Hydrochlorothiazide is not metabolized. Its apparent volume of distribution is 3.6 to 7.8 L/kg, and its measured plasma protein binding is 67.9%. The drug also accumulates in red blood cells, so that whole blood levels are 1.6 to 1.8 times those measured in plasma.

After intravenous administration, fosinoprilat is eliminated approximately equally by the liver and kidney. After oral administration of radiolabeled fosinopril, approximately half of the absorbed dose is excreted in the urine and the remainder is excreted in the feces. In two studies involving healthy subjects, the mean body clearance of intravenous fosinoprilat was between 26 and 39 mL/min.

In hypertensive patients with normal renal and hepatic function, the effective half-life of accumulation of fosinoprilat following multiple dosing of fosinopril sodium is 11.5 hours. Thus, steady-state concentrations of fosinoprilat should be reached after 2 or 3 doses of fosinopril sodium and hydrochlorothiazide given once daily.

In patients with renal insufficiency (creatinine clearance <80 mL/min/1.73 m^2), the total body clearance of fosinoprilat is approximately one half of that in patients with normal renal function, while absorption, bioavailability, and protein binding are not appreciably altered. The clearance of fosinoprilat does not differ appreciably with the degree of renal insufficiency, because the diminished renal elimination is offset by increased hepatobiliary elimination. A modest increase in plasma AUC levels (less than two times that in normals) was observed in patients with various degrees of renal insufficiency, including end-stage renal failure (creatinine clearance <10 mL/min/1.73 m^2). (See DOSAGE AND ADMINISTRATION.)

Fosinopril is not well dialyzed. Clearance of fosinoprilat by hemodialysis and peritoneal dialysis averages 2% and 7%, respectively, of urea clearances.

In patients with hepatic insufficiency (alcoholic or biliary cirrhosis), the apparent total body clearance of fosinoprilat is approximately one half of that in patients with normal hepatic function.

In elderly (male) subjects (65 to 74 years old) with clinically normal renal and hepatic function, there appear to be no significant differences in pharmacokinetic parameters for fosinoprilat compared to those of younger subjects (20 to 35 years old).

Thiazide diuretics are eliminated by the kidney, with a terminal half-life of 5 to 15 hours. In a study of patients with impaired renal function (mean creatinine clearance of 19 mL/min), the half-life of hydrochlorothiazide elimination was lengthened to 21 hours.

When fosinopril and hydrochlorothiazide are administered concomitantly, the pharmacokinetics of hydrochlorothiazide are essentially unaffected. Serum levels of fosinoprilat are increased after several weeks of coadministration of hydrochlorothiazide and fosinopril, but the increase is not sufficient to warrant any change in dosing.

Pharmacodynamics

After single doses of 10 to 40 mg of fosinopril, serum ACE activity was inhibited by at least 90% from 2 to 12 hours after dosing. At 24 hours, serum ACE activity remains suppressed by 85 to 93%.

Administration of fosinopril to patients with mild to moderate hypertension results in a reduction of both supine and standing blood pressure to about the same extent with no compensatory tachycardia. In studies in hypertensive patients after three months of fosinopril monotherapy, hemodynamic responses to various stimuli (isometric exercise, 45° head-up tilt, mental challenges) were unchanged compared to baseline, suggesting that fosinopril did not affect the activity of the sympathetic nervous system. Instead, fosinopril-induced reduction in blood pressure appears to be mediated by a reduction in peripheral vascular resistance without reflex cardiac effects. In similar studies, renal, splanchnic, cerebral, and skeletal-muscle blood flows were all unchanged compared to baseline, as was glomerular filtration rate. Symptomatic postural hypotension is infrequent, although it can occur in patients who are salt- and/or volume-depleted (see WARNINGS).

Following oral administration of single doses of 10 to 40 mg, fosinopril lowered blood pressure within one hour, with peak reductions achieved 2 to 6 hours after dosing. The antihypertensive effect of a single dose persisted for 24 hours. Following four weeks of monotherapy in placebo-controlled trials in patients with mild to moderate hypertension, once-daily doses of 20 to 80 mg lowered supine or seated blood pressures (systolic/diastolic) 24 hours after dosing by an average of 8 to 9/6 to 7 mmHg more than placebo. The trough effect was about 50 to 60% of the peak diastolic response and about 80% of the peak systolic response.

In clinical studies of various combinations that included 0 to 40 mg of fosinopril and 0 to 37.5 mg of hydrochlorothiazide, the antihypertensive effects were increased with increasing dose of either component. Peak blood pressure reductions were achieved 2 to 6 hours after dosing. The mean reductions in seated blood pressure (systolic/diastolic) associated with fosinopril sodium and hydrochlorothiazide tablets 10/12.5 after 24 hours were 9 to 18/5 to 7 mmHg greater than those associated with placebo; those associated with fosinopril sodium and hydrochlorothiazide 20/12.5 after 24 hours were 12 to 17/8 to 10 mmHg greater than those associated with placebo. These trough effects were 60 to 90% of the corresponding peak effects.

Although hydrochlorothiazide tends to be more effective in low-renin hypertensive patients (mainly blacks), and fosinopril—like other ACE inhibitors—tends to be more effective in high-renin patients (mainly non-blacks), the effectiveness of fosinopril sodium and hydrochlorothiazide is independent of race, age, and gender.

INDICATIONS AND USAGE

Fosinopril sodium and hydrochlorothiazide tablets are indicated for the treatment of hypertension.

These fixed dose combinations are not indicated for initial therapy. (See DOSAGE AND ADMINISTRATION.)

In using fosinopril sodium and hydrochlorothiazide, consideration should be given to the fact that another angiotensin-converting enzyme inhibitor, captopril, has caused agranulocytosis, particularly in patients with renal impairment or collagen-vascular disease. Available data are insufficient to show that fosinopril does not have a similar risk (see WARNINGS: Neutropenia/Agranulocytosis).

ACE inhibitors (for which adequate data are available) cause a higher rate of angioedema in black than in non-black patients (see WARNINGS: Head and Neck Angioedema and Intestinal Angioedema).

CONTRAINDICATIONS

Fosinopril sodium and hydrochlorothiazide tablets are contraindicated in patients who are anuric. Fosinopril sodium and hydrochlorothiazide is also contraindicated in patients who are hypersensitive to fosinopril, to any other ACE inhibitor, to hydrochlorothiazide, or other sulfonamide-derived drugs, or any other ingredient or component in the formulation. Hypersensitivity reactions are more likely to occur in patients with a history of allergy or bronchial asthma.

WARNINGS

Anaphylactoid and Possibly Related Reactions

Presumably because angiotensin-converting enzyme inhibitors affect the metabolism of eicosanoids and polypeptides, including endogenous bradykinin, patients receiving ACE inhibitors (including fosinopril sodium and hydrochlorothiazide) may be subject to a variety of adverse reactions, some of them serious.

Head and Neck Angioedema

Angioedema of the face, extremities, lips, tongue, glottis, and larynx has been reported in patients treated with angiotensin-converting enzyme inhibitors. Angioedema associated with laryngeal edema can be fatal. If laryngeal stridor or angioedema of the face, tongue, or glottis occurs, treatment with fosinopril sodium and hydrochlorothiazide should be discontinued and appropriate therapy instituted immediately. When involvement of the tongue, glottis, or larynx appears likely to cause airway obstruction, appropriate therapy, e.g., subcutaneous epinephrine injection 1:1000 (0.3 to 0.5 mL) should be promptly administered (see PRECAUTIONS and ADVERSE REACTIONS).

Intestinal Angioedema

Intestinal angioedema has been reported in patients treated with ACE inhibitors. These patients presented with abdominal pain (with or without nausea or vomiting); in some cases there was no prior history of facial angioedema and C-1 esterase levels were normal. The angioedema was diagnosed by procedures including abdominal CT scan or ultrasound, or at surgery, and symptoms resolved after stopping the ACE inhibitor. Intestinal angioedema should be included in the differential diagnosis of patients on ACE inhibitors presenting with abdominal pain.

Anaphylactoid Reactions During Desensitization

Two patients undergoing desensitizing treatment with hymenoptera venom while receiving ACE inhibitors sustained life-threatening anaphylactoid reactions. In the same patients, these reactions were avoided when ACE inhibitors were temporarily withheld, but they reappeared upon inadvertent rechallenge.

Anaphylactoid Reactions During Membrane Exposure

Anaphylactoid reactions have been reported in patients dialyzed with high-flux membranes and treated concomitantly with an ACE inhibitor. Anaphylactoid reactions have also been reported in patients undergoing low-density lipoprotein apheresis with dextran sulfate absorption.

Hypotension

Fosinopril sodium and hydrochlorothiazide can cause symptomatic hypotension. Like other ACE inhibitors, fosinopril has been only rarely associated with hypotension in uncomplicated hypertensive patients. Symptomatic hypotension is most likely to occur in patients who have been volume- and/or salt-depleted as a result of prolonged diuretic therapy, dietary salt restriction, dialysis, diarrhea, or vomiting. Volume and/or salt depletion should be corrected before initiating therapy with fosinopril sodium and hydrochlorothiazide.

Fosinopril sodium and hydrochlorothiazide tablets should be used cautiously in patients receiving concomitant therapy with other antihypertensives. The thiazide component of fosinopril sodium and hydrochlorothiazide may potentiate the action of other antihypertensive drugs, especially ganglionic or peripheral adrenergic-blocking drugs. The antihypertensive effects of the thiazide component may also be enhanced in the post-sympathectomy patient.

In patients with congestive heart failure, with or without associated renal insufficiency, ACE inhibitor therapy may cause excessive hypotension, which may be associated with oliguria, azotemia, and (rarely) with acute renal failure and death. In such patients, fosinopril sodium and hydrochlorothiazide therapy should be started under close medical supervision; they should be followed closely for the first 2 weeks of treatment and whenever the dose of fosinopril or diuretic is increased.

If hypotension occurs, the patient should be placed in a supine position, and, if necessary, treated with intravenous infusion of physiological saline. Fosinopril sodium and hydrochlorothiazide treatment usually can be continued following restoration of blood pressure and volume.

Impaired Renal Function

Fosinopril sodium and hydrochlorothiazide should be used with caution in patients with severe renal disease. Thiazides may precipitate azotemia in such patients, and the effects of repeated dosing may be cumulative.

When the renin-angiotensin-aldosterone system is inhibited by ACE inhibitors, changes in renal function may be anticipated in susceptible individuals. In patients with severe congestive heart failure, whose renal function may depend on the activity of the renin-angiotensin-aldosterone system, treatment with angiotensin-converting enzyme inhibitors (including fosinopril) may be associated with oliguria and/or progressive azotemia and (rarely) with acute renal failure and/or death.

In some studies of hypertensive patients with unilateral or bilateral renal artery stenosis, treatment with ACE inhibitors has been associated with increases in blood urea nitrogen and serum creatinine; these increases were reversible upon discontinuation of ACE inhibitor therapy, concomitant diuretic therapy, or both. When such patients are treated with fosinopril sodium and hydrochlorothiazide, renal function should be monitored during the first few weeks of therapy.

Some ACE-inhibitor-treated hypertensive patients with no apparent preexisting renal vascular disease have developed increases in blood urea nitrogen and serum creatinine, usually minor and transient, especially when the ACE inhibitor has been given concomitantly with a diuretic. Dosage reduction of fosinopril sodium and hydrochlorothiazide may be required. Evaluation of the hypertensive patient should always include assessment of renal function (see DOSAGE AND ADMINISTRATION).

Neutropenia/Agranulocytosis

Another angiotensin-converting enzyme inhibitor, captopril, has been shown to cause agranulocytosis and bone marrow depression, rarely in uncomplicated patients (incidence probably less than once per 10,000 exposures), but more frequently (incidence possibly as great as once per 1,000 exposures) in patients with renal impairment, especially those who also have a collagen-vascular disease such as systemic lupus erythematosus or scleroderma. Available data from clinical trials of fosinopril are insufficient to show that fosinopril does not cause agranulocytosis at similar rates. Monitoring of white blood cell counts should be considered in patients with collagen-vascular disease, especially if the disease is associated with impaired renal function.

Neutropenia/agranulocytosis has also been associated with thiazide diuretics.

Fetal Toxicity

Pregnancy Category D

Use of drugs that act on the renin-angiotensin system during the second and third trimesters of pregnancy reduces fetal renal function and increases fetal and neonatal morbidity and death. Resulting oligohydramnios can be associated with fetal lung hypoplasia and skeletal deformations. Potential neonatal adverse effects include skull hypoplasia, anuria, hypotension, renal failure, and death. When pregnancy is detected, discontinue fosinopril and hydrochlorothiazide as soon as possible. These adverse outcomes are usually associated with use of these drugs in the second and third trimester of pregnancy. Most epidemiologic studies examining fetal abnormalities after exposure to antihypertensive use in the first trimester have not distinguished drugs affecting the renin-angiotensin system from other antihypertensive agents. Appropriate management of maternal hypertension during pregnancy is important to optimize outcomes for both mother and fetus.

In the unusual case that there is no appropriate alternative to therapy with drugs affecting the renin-angiotensin system for a particular patient, apprise the mother of the potential risk to the fetus. Perform serial ultrasound examinations to assess the intra-amniotic environment. If oligohydramnios is observed, discontinue fosinopril and hydrochlorothiazide, unless it is considered lifesaving for the mother. Fetal testing may be appropriate, based on the week of pregnancy. Patients and physicians should be aware, however, that oligohydramnios may not appear until after the fetus has sustained irreversible injury. Closely observe infants with histories of in utero exposure to fosinopril and hydrochlorothiazide for hypotension, oliguria, and hyperkalemia (see PRECAUTIONS, Pediatric Use).

Intrauterine exposure to thiazide diuretics is associated with fetal or neonatal jaundice, thrombocytopenia, and possibly other adverse reactions that occurred in adults.

No teratogenic effects of fosinopril were seen in studies of pregnant rats and rabbits. On a mg/kg basis, the doses used were up to 180 times (in rats) and one time (in rabbits) the maximum recommended human dose. No teratogenic effects of fosinopril and hydrochlorothiazide were seen in studies of pregnant rats and rabbits. On a mg/kg (fosinopril and hydrochlorothiazide) basis, the doses used were up to 188/94 times (in rats) and 0.6/0.3 times (in rabbits) the maximum recommended human dose.

Impaired Hepatic Function

Rarely, ACE inhibitors have been associated with a syndrome that begins with cholestatic jaundice and progresses to fulminant hepatic necrosis and (sometimes) death. The mechanism of this syndrome is not understood. A patient receiving fosinopril sodium and hydrochlorothiazide who develops jaundice or marked elevation of hepatic enzymes should discontinue fosinopril sodium and hydrochlorothiazide tablets and receive appropriate medical follow-up.

Fosinopril sodium and hydrochlorothiazide should be used with caution in patients with impaired hepatic function or progressive liver disease, since minor alterations of fluid and electrolyte balance may precipitate hepatic coma. Also, since the metabolism of fosinopril to fosinoprilat is normally dependent upon hepatic esterases, patients with impaired liver function could develop elevated plasma levels of fosinopril. In a study of patients with alcoholic or biliary cirrhosis the rate (but not the extent) of hydrolysis to fosinoprilat was reduced. In these patients the clearance of fosinoprilat was reduced, and the area under the fosinoprilat-time curve was approximately doubled.

Systemic Lupus Erythematosus

Thiazide diuretics have been reported to cause exacerbation or activation of systemic lupus erythematosus.

PRECAUTIONS

General

Derangements of Serum Electrolytes

In clinical trials of fosinopril monotherapy, hyperkalemia (serum potassium at least 10% greater than the upper limit of normal) occurred in approximately 2.6% of hypertensive patients receiving fosinopril. In most cases, these were isolated values which resolved despite continued therapy. Risk factors for the development of hyperkalemia included renal insufficiency, diabetes mellitus, and the concomitant use of potassium-sparing diuretics, potassium supplements, and/or potassium-containing salt substitutes.

Conversely, treatment with thiazide diuretics has been associated with hypokalemia, hyponatremia, and hypochloremic alkalosis. These disturbances have sometimes been manifest as one or more of dryness of mouth, thirst, weakness, lethargy, drowsiness, restlessness, muscle pains or cramps, muscular fatigue, hypotension, oliguria, tachycardia, nausea, and vomiting. Hypokalemia can also sensitize or exaggerate the response of the heart to the toxic effects of digitalis. The risk of hypokalemia is greatest in patients with cirrhosis of the liver, in patients experiencing a brisk diuresis, in patients who are receiving inadequate oral intake of electrolytes, and in patients receiving concomitant therapy with corticosteroids or ACTH.

The opposite effects of fosinopril and hydrochlorothiazide on serum potassium will approximately balance each other in many patients, so that no net effect upon serum potassium will be seen. In other patients, one or the other effect may be dominant. Initial and periodic determinations of serum electrolytes to detect possible electrolyte imbalance should be performed at appropriate intervals.

Chloride deficits are generally mild and require specific treatment only under extraordinary circumstances (e.g., in liver disease or renal disease). Dilutional hyponatremia may occur in edematous patients; appropriate therapy is water restriction rather than administration of salt, except in rare instances when the hyponatremia is life-threatening. In actual salt depletion, appropriate replacement is the therapy of choice.

Calcium excretion is decreased by thiazides. In a few patients on prolonged thiazide therapy, pathological changes in the parathyroid gland have been observed, with hypercalcemia and hypophosphatemia. More serious complications of hyperparathyroidism (renal lithiasis, bone resorption, and peptic ulceration) have not been seen.

Thiazides increase the urinary excretion of magnesium, and hypomagnesemia may result.

Other Metabolic Disturbances

Thiazide diuretics tend to reduce glucose tolerance and to raise serum levels of cholesterol, triglycerides, and uric acid. These effects are usually minor, but frank gout or overt diabetes may be precipitated in susceptible patients.

Cough

Presumably due to the inhibition of the degradation of endogenous bradykinin, persistent nonproductive cough has been reported with all ACE inhibitors, always resolving after discontinuation of therapy. ACE inhibitor-induced cough should be considered in the differential diagnosis of cough.

Surgery/Anesthesia

In patients undergoing surgery or during anesthesia with agents that produce hypotension, fosinopril will block the angiotensin II formation that could otherwise occur secondary to compensatory renin release. Hypotension that occurs as a result of this mechanism can be corrected by volume expansion.

Information for Patients

Angioedema

Angioedema, including laryngeal edema, can occur with treatment with ACE inhibitors, especially following the first dose. A patient receiving fosinopril sodium and hydrochlorothiazide should be told to report immediately any signs or symptoms suggesting angioedema (swelling of face, eyes, lips, or tongue, or difficulty in breathing) and to take no more drug until after consulting with the prescribing physician.

Pregnancy

Female patients of childbearing age should be told about the consequences of exposure to fosinopril and hydrochlorothiazide during pregnancy. Discuss treatment options with women planning to become pregnant. Patients should be asked to report pregnancies to their physicians as soon as possible.

Symptomatic Hypotension

A patient receiving fosinopril sodium and hydrochlorothiazide tablets should be cautioned that lightheadedness can occur, especially during the first days of therapy, and that it should be reported to the prescribing physician. The patients should be told that if syncope occurs, fosinopril sodium and hydrochlorothiazide should be discontinued until the physician has been consulted.

All patients should be cautioned that inadequate fluid intake, excessive perspiration, diarrhea, or vomiting can lead to an excessive fall in blood pressure, with the same consequences of lightheadedness and possible syncope.

Hyperkalemia

A patient receiving fosinopril sodium and hydrochlorothiazide should be told not to use potassium supplements or salt substitutes containing potassium without consulting the prescribing physician.

Neutropenia

Patients should be told to promptly report any indication of infection (e.g., sore throat, fever), which could be a sign of neutropenia.

DRUG AND OR LABORATORY TEST INTERACTIONS

Non-melanoma Skin Cancer: Instruct patients taking hydrochlorothiazide to protect skin from the sun and undergo regular skin cancer screening.

Laboratory Tests

Therapy with fosinopril sodium and hydrochlorothiazide should be interrupted for a few days before carrying out tests of parathyroid function.

Fosinopril may cause false low measurement of serum digoxin levels when the Digi-Tab® (Nuclear Medical) RIA Kit is used. The accuracy of the Coat-A-Count® (Diagnostic Products Corporation) kit is not affected.

Drug Interactions

Potassium supplements and potassium-sparing diuretics

As noted above (“Derangements of Serum Electrolytes”), the net effect of fosinopril sodium and hydrochlorothiazide may be to elevate a patient’s serum potassium, to reduce it, or to leave it unchanged. Potassium-sparing diuretics (spironolactone, amiloride, triamterene, and others) or potassium supplements can increase the risk of hyperkalemia. If concomitant use of such agents is indicated, they should be given with caution, and the patient’s serum potassium should be monitored frequently.

Lithium

Increased serum lithium levels and symptoms of lithium toxicity have been reported in patients receiving ACE inhibitors during therapy with lithium. Because renal clearance of lithium is reduced by thiazides, the risk of lithium toxicity is presumably raised further when, as in therapy with fosinopril sodium and hydrochlorothiazide tablets, a thiazide diuretic is coadministered with the ACE inhibitor. Fosinopril sodium and hydrochlorothiazide and lithium should be coadministered with caution, and frequent monitoring of serum lithium levels is recommended.

Antacids

In a clinical pharmacology study, serum levels and urinary excretion of fosinoprilat were reduced when fosinopril was coadministered with an antacid (aluminum hydroxide, magnesium hydroxide, and simethicone) suggesting that antacids may impair absorption of fosinopril. If concomitant administration of these agents is indicated, dosing should be separated by 2 hours.

Gold

Nitritoid reactions (symptoms include facial flushing, nausea, vomiting, and hypotension) have been reported rarely in patients on therapy with injectable gold (sodium aurothiomalate) and concomitant ACE Inhibitor therapy including fosinopril sodium and hydrochlorothiazide.

Other

The bioavailability of unbound fosinoprilat is not altered by coadministration of fosinopril with aspirin, chlorthalidone, cimetidine, digoxin, metoclopramide, nifedipine, propranolol, propantheline, or warfarin. Other ACE inhibitors have had less than additive effects with beta-adrenergic blockers, presumably because drugs of both classes lower blood pressure by inhibiting parts of the renin-angiotensin system.

Interaction studies with warfarin have failed to identify any clinically important effects of fosinopril on the serum concentration or clinical effects of the anticoagulant.

Insulin requirements in diabetic patients may be increased, decreased, or unchanged.

Thiazides may decrease arterial responsiveness to norepinephrine, but not enough to preclude effectiveness of the pressor agent for therapeutic use.

Thiazides may increase the responsiveness to tubocurarine.

The diuretic, natriuretic, and antihypertensive effects of thiazide diuretics may be reduced by concurrent administration of nonsteroidal anti-inflammatory agents; the effects (if any) of these agents on the antihypertensive effect of fosinopril sodium and hydrochlorothiazide have not been studied.

By alkalinizing the urine, hydrochlorothiazide may decrease the effectiveness of methenamine.

Cholestyramine and Colestipol Resins

Absorption of hydrochlorothiazide is impaired in the presence of anionic exchange resins. Single doses of either cholestyramine or colestipol resins bind the hydrochlorothiazide and reduce its absorption from the gastrointestinal tract by up to 85% and 43%, respectively.
Dual Blockade of the Renin-Angiotensin System (RAS)
Dual blockade of the RAS with angiotensin receptor blockers, ACE inhibitors, or aliskiren is associated with increased risks of hypotension, hyperkalemia, and changes in renal function (including acute renal failure) compared to monotherapy. Closely monitor blood pressure, renal function and electrolytes in patients on fosinopril and hydrochlorothiazide and other agents that affect the RAS.
Do not co-administer aliskiren with fosinopril and hydrochlorothiazide in patients with diabetes. Avoid use of aliskiren with fosinopril and hydrochlorothiazide in patients with renal impairment (GFR <60 mL/min).

Carcinogenesis, Mutagenesis, Impairment of Fertility

Fosinopril-Hydrochlorothiazide

Reproductive studies and long-term carcinogenicity studies with fosinopril sodium and hydrochlorothiazide have not been conducted. The combination of fosinopril and hydrochlorothiazide was not mutagenic in the Ames microbial mutagen test, the mouse lymphoma forward mutation assay, or the Chinese hamster ovary cell cytogenetic assay. The combination was also not genotoxic in a mouse micronucleus test in vivo.

Fosinopril Sodium

No evidence of a carcinogenicity was found when fosinopril was given in the diet to rats and mice for up to 24 months at doses up to 400 mg/kg/day. On a body weight basis, the highest dose was about 250 times the maximum human dose of 80 mg, given to a 50 kg subject. On a body surface area basis, this dose is 20 (mice) to 40 (rats) times the maximum human dose.

Neither fosinopril nor the fosinoprilat moiety was mutagenic in the Ames microbial mutagen test, the mouse lymphoma forward mutation assay, or a mitotic gene conversion assay. Fosinopril was also not genotoxic in a mouse micronucleus test in vivo and a mouse bone marrow cytogenetic assay in vivo.

In Chinese hamster ovary cell cytogenetic assay, fosinopril increased the frequency of chromosomal aberrations when tested without metabolic activation at a concentration that was toxic to the cells. However, there was no increase in chromosomal aberrations at lower drug concentrations without metabolic activation or at any concentration with metabolic activation.

There were no adverse reproductive effects in male and female rats treated with up to 60 mg/kg daily. At doses 4 times higher, slight increases in pairing time were seen. This higher dose is about 125 (body surface area basis) or 600 (body-weight basis) times greater than the dose received by a 50 kg human receiving 20 mg a day.

Hydrochlorothiazide

Under the auspices of the National Toxicology Program, rats and mice received hydrochlorothiazide for two years at doses up to 100 (rats) and 600 (mice) mg/kg/day. On a body weight basis, these highest doses were about 2400 times (mice) or 400 times (rats) the fosinopril sodium and hydrochlorothiazide dose of 12.5 mg, given to a 50 kg subject. On a body surface area basis, these doses are 226 times (mice) and 82 times (rats) the fosinopril sodium and hydrochlorothiazide dose. These studies uncovered no evidence of carcinogenicity in rats or female mice, but there was equivocal evidence of hepatocarcinogenicity in male mice.

Hydrochlorothiazide was not genotoxic in in vitro assays using strains TA 98, TA 100, TA 1535, TA 1537, and TA 1538 of Salmonella typhimurium (Ames assay); in the Chinese Hamster Ovary (CHO) test for chromosomal aberrations; or in in vivo assays using mouse germinal cell chromosomes; Chinese Hamster bone-marrow chromosomes, and the Drosophila sex-linked recessive lethal trait gene. Using concentrations of hydrochlorothiazide of 43 to 1300 mg/mL, positive test results were obtained in the in vitro CHO Sister Chromatid Exchange (clastogenicity) test and in the Mouse Lymphoma Cell (mutagenicity) assays. Using an unspecified concentration of hydrochlorothiazide, positive test results were also obtained in the Aspergillus nidulans nondisjunction assay.

No adverse effects upon fertility were seen when rats and mice received dietary hydrochlorothiazide prior to mating and throughout gestation at doses up to 4 (rats) and 100 (mice) mg/kg/day. These doses are from 3.2 (body surface area basis in rats) to 400 (weight basis in mice) times greater than the dose received by a 50 kg human receiving 12.5 mg a day.

Nursing Mothers

Both fosinopril and hydrochlorothiazide are excreted in human milk. Because of the potential for serious adverse reactions in nursing infants, a decision should be made whether to discontinue nursing or to discontinue fosinopril sodium and hydrochlorothiazide, taking into account the importance of the drug to the mother.

Geriatric Use

Clinical studies of fosinopril sodium and hydrochlorothiazide did not include sufficient numbers of subjects aged 65 and over to determine whether they respond differently from younger subjects. Other reported clinical experience has not identified differences in responses between elderly and younger patients. In general, dose selection for an elderly patient should be cautious, usually starting at the low end of the dosing range, reflecting the greater frequency of decreased hepatic, renal, or cardiac function, and of concomitant disease or other drug therapy.

Pediatric Use

Neonates with a history of in utero exposure to fosinopril and hydrochlorothiazide:

If oliguria or hypotension occurs, direct attention toward support of blood pressure and renal perfusion. Exchange transfusions or dialysis may be required as a means of reversing hypotension and/or substituting for disordered renal function. Removal of fosinopril and hydrochlorothiazide, which crosses the placenta, from the neonatal circulation is not significantly accelerated by these means.

Safety and effectiveness in pediatric patients have not been established.

ADVERSE REACTIONS

Fosinopril sodium and hydrochlorothiazide tablets have been evaluated for safety in over 660 patients with hypertension; approximately 137 of these patients were treated for more than one year. The observed adverse events were generally mild, transient, and similar to those seen with fosinopril and hydrochlorothiazide taken separately. There was no relationship between the incidence of side effects and age.

In placebo-controlled clinical trials of fosinopril sodium and hydrochlorothiazide, the usual duration of therapy was two months. Adverse clinical or laboratory events led to discontinuation of therapy by 4.3% of 368 placebo-treated patients and by 3.5% of 660 fosinopril sodium and hydrochlorothiazide-treated patients.

The most common reasons for discontinuation of therapy with fosinopril sodium and hydrochlorothiazide in U.S. studies were headache (0.3%), cough (0.3%; see PRECAUTIONS), and fatigue (0.2%).

The side effects considered probably or possibly related to study drug that occurred in placebo-controlled trials in more than 2% of patients treated with fosinopril sodium and hydrochlorothiazide are shown in the table below.

Reactions Possibly or Probably Drug-Related (Incidence in Placebo-Controlled Studies)
 | Fosinopril Sodium and Hydrochlorothiazide (N=660) | Placebo (N=368)
 | % | %
Headache | 7 | 12.8
Cough | 5.6 | 1.1
Fatigue | 3.9 | 2.4
Dizziness | 3.2 | 2.2
Upper Respiratory Infection | 2.3 | 2.7
Musculoskeletal Pain | 2 | 1.9

Other side effects considered possibly or probably related to study drug that occurred in controlled trials in 0.5% to <2% of patients treated with fosinopril sodium and hydrochlorothiazide, and rarer but clinically significant events regardless of causal relationship were:
General: Chest pain, weakness, fever, viral infection.
Cardiovascular: Orthostatic hypotension (seen in 1.8% of fosinopril sodium and hydrochlorothiazide patients and 0.3% of placebo patients; no patients discontinued therapy due to orthostatic hypotension), edema, flushing, rhythm disturbance, syncope.
Dermatologic: Pruritus, rash.
Endocrine/Metabolic: Sexual dysfunction, change in libido, breast mass.
Gastrointestinal: Nausea/vomiting, diarrhea, dyspepsia/heartburn, abdominal pain, gastritis/esophagitis.
Immunologic: Angioedema (see WARNINGS: Head and Neck Angioedema and Intestinal Angioedema).
Musculoskeletal: Myalgia/muscle cramps.
Neurologic/Psychiatric: Somnolence, depression, numbness/paresthesia.
Respiratory: Sinus congestion, pharyngitis, rhinitis.
Special Senses: Tinnitus.
Urogenital: Urinary tract infection, urinary frequency, dysuria.

Laboratory Test Abnormalities: Serum electrolytes, uric acid, glucose, magnesium, cholesterol, triglycerides, and calcium (see PRECAUTIONS). Neutropenia.

Antihypertensive monotherapy with fosinopril has been evaluated for safety in more than 1500 patients, of whom approximately 450 patients were treated for a year or more. The observed adverse events included events similar to those seen with fosinopril sodium and hydrochlorothiazide; in addition, the following others have also been reported with fosinopril:

Cardiovascular: Angina, myocardial infarction, cerebrovascular accident, hypertensive crisis, hypotension, claudication.

Dermatologic: Urticaria, photosensitivity.

Endocrine/Metabolic: Gout.

Gastrointestinal: Pancreatitis, hepatitis, dysphagia, abdominal distention, flatulence, appetite/weight change, dry mouth.

Hematologic: Lymphadenopathy.

Musculoskeletal: Arthralgia.

Neurologic/Psychiatric: Memory disturbance, tremor, confusion, mood change, sleep disturbance.

Respiratory: Bronchospasm, laryngitis/hoarseness, epistaxis, and (in two patients) a symptom-complex of cough, bronchospasm, and eosinophilia.

Special Senses: Vision disturbance, taste disturbance, eye irritation.

Urogenital: Renal insufficiency.

Laboratory Test Abnormalities: Elevations (usually transient and minor) of BUN and creatinine have been observed, but these have not been more frequent than in parallel patients treated with placebo. The hemoglobin in fosinopril-treated patients generally decreases by an average of 0.1 g/dL, but this nonprogressive change has never been symptomatic. Leukopenia and eosinophilia have also been reported.

Serum levels of liver function tests (transaminases, LDH, alkaline phosphatase and serum bilirubin) have occasionally been found to be elevated, and these elevations have lead to discontinuation of therapy in 0.7% of patients. Other risk factors for liver dysfunction have often been present in these cases; in any event the elevations generally have resolved after discontinuation of therapy with fosinopril.

Other Adverse Events Reported with ACE Inhibitors

Other adverse effects reported with ACE inhibitors include cardiac arrest; pancytopenia, hemolytic anemia; aplastic anemia; thrombocytopenia; bullous pemphigus, exfoliative dermatitis; and a syndrome that may include one or more of arthralgia/arthritis, vasculitis, serositis, myalgia, fever, rash or other dermopathy, positive ANA titer, leukocytosis, eosinophilia, and elevated ESR.

Hydrochlorothiazide has now been extensively prescribed for many years, but there has not been enough systematic collection of data to support an estimate of the frequency of the observed adverse reactions. Within organ-system groups, the reported reactions are listed here in decreasing order of severity, without regard to frequency.

Cardiovascular: Orthostatic hypotension (may be potentiated by alcohol, barbiturates, or narcotics).
Gastrointestinal: Pancreatitis, jaundice (intrahepatic cholestatic), sialadenitis, vomiting, diarrhea, cramping, nausea, gastric irritation, constipation, and anorexia.
Hematologic: Aplastic anemia, agranulocytosis, leukopenia, thrombocytopenia, and hemolytic anemia.
Immunologic: Necrotizing angiitis, Stevens-Johnson syndrome, respiratory distress (including pneumonitis and pulmonary edema), anaphylactic reactions, purpura, urticaria, rash, and photosensitivity.
Metabolic: Hyperglycemia, glycosuria, and hyperuricemia.
Musculoskeletal: Muscle spasm.
Neurologic: Vertigo, lightheadedness, transient blurred vision, headache, paresthesia, xanthopsia, weakness, and restlessness.
Non-melanoma Skin Cancer

Hydrochlorothiazide is associated with an increased risk of non-melanoma skin cancer. In a study conducted in the Sentinel System, increased risk was predominantly for squamous cell carcinoma (SCC) and in white patients taking large cumulative doses. The increased risk for SCC in the overall population was approximately 1 additional case per 16,000 patients per year, and for white patients taking a cumulative dose of ≥50,000mg the risk increase was approximately 1 additional SCC case for every 6,700 patients per year.

OVERDOSAGE

To obtain up-to-date information about the treatment of overdose, a good resource is a certified Regional Poison Control Center. Telephone numbers of certified poison control centers are listed in the Physicians’ Desk Reference (PDR). In managing overdose, consider the possibilities of multiple-drug overdoses, drug-drug interactions, and unusual drug kinetics in your patient.

No specific information is available on the treatment of overdosage with fosinopril sodium and hydrochlorothiazide tablets; treatment should be symptomatic and supportive. Therapy with fosinopril sodium and hydrochlorothiazide should be discontinued, and the patient should be observed. Dehydration, electrolyte imbalance, and hypotension should be treated by established procedures.

In rats, single oral doses of 2600 mg/kg of fosinopril were associated with significant lethality. In single-dose studies of hydrochlorothiazide, most rats survived doses of up to 2750 mg/kg. Both doses are more than 6000 times (on a mg/kg basis) the maximum recommended daily dose of either fosinopril or hydrochlorothiazide in fosinopril sodium and hydrochlorothiazide.

Data from human overdoses of fosinopril are scanty, but the most common manifestation of human fosinopril overdosage is likely to be hypotension. In human hydrochlorothiazide overdose, the most common signs and symptoms observed have been those of dehydration and electrolyte depletion (hypokalemia, hypochloremia, hyponatremia). If digitalis has also been administered, hypokalemia may accentuate cardiac arrhythmias.

Laboratory determinations of serum levels of fosinopril and its metabolites are not widely available, and such determinations have, in any event, no established role in the management of fosinopril overdose. No data are available to suggest physiological maneuvers (e.g., maneuvers to change the pH of the urine) that might accelerate elimination of fosinopril and its metabolites. Fosinoprilat is poorly removed from the body by hemodialysis or peritoneal dialysis.

Angiotensin II could presumably serve as a specific antagonist-antidote in the setting of fosinopril overdose, but angiotensin II is essentially unavailable outside of scattered research facilities. Because the hypotensive effect of fosinopril is achieved through vasodilation and effective hypovolemia, it is reasonable to treat fosinopril overdose by infusion of normal saline solution.

DOSAGE AND ADMINISTRATION

Fosinopril is an effective treatment of hypertension in once-daily doses of 10 to 80 mg, while hydrochlorothiazide is effective in doses of 12.5 to 50 mg per day. In clinical trials of fosinopril/hydrochlorothiazide combination therapy using fosinopril doses of 2.5 to 40 mg and hydrochlorothiazide doses at 5 to 37.5 mg, the antihypertensive effects increased with increasing dose of either component.

The hazards (see WARNINGS) of fosinopril are generally rare and apparently independent of dose; those of hydrochlorothiazide are a mixture of dose-dependent phenomena (primarily hypokalemia) and dose-independent phenomena (e.g., pancreatitis), the former much more common than the latter. Therapy with any combination of fosinopril and hydrochlorothiazide will be associated with both sets of dose-independent hazards. To minimize dose-independent hazards, it is usually appropriate to begin combination therapy only after a patient has failed to achieve the desired effect with monotherapy.

Dose Titration by Clinical Effect

A patient whose blood pressure is not adequately controlled with fosinopril or hydrochlorothiazide monotherapy may be switched to combination therapy with fosinopril sodium and hydrochlorothiazide tablets. Dosage must be guided by clinical response; controlled clinical trials showed that the addition of 12.5 mg of hydrochlorothiazide to 10 to 20 mg of fosinopril will typically be associated with additional reduction in seated diastolic blood pressure at 24 hours after dosing. On average, the effect of the combination of 10 mg of fosinopril with 12.5 mg of hydrochlorothiazide was similar to the effect seen with monotherapy using either 40 mg of fosinopril or 37.5 mg of hydrochlorothiazide.

Use in Renal Impairment

In patients with severe renal impairment (creatinine clearance is <30 mL/min/1.73 m^2, serum creatine roughly ≥3 mg/dL or 265 µmol/L), loop diuretics are preferred to thiazides, so fosinopril sodium and hydrochlorothiazide tablets are not recommended. In patients with lesser degrees of renal impairment, fosinopril sodium and hydrochlorothiazide tablets may be used with no change in dosage.

HOW SUPPLIED

Fosinopril Sodium and Hydrochlorothiazide Tablets USP, 10 mg/12.5 mg are peach colored, round biconvex, uncoated tablets debossed with ‘C 84’ on one side and plain on the other side.
Bottle of 30 NDC 65862-308-30
Bottle of 100 NDC 65862-308-01
Bottle of 1,000 NDC 65862-308-99
Fosinopril Sodium and Hydrochlorothiazide Tablets USP, 20 mg/12.5 mg are peach colored, round biconvex, uncoated tablets debossed with ‘C 85’ on one side and “deep score line” on the other side.
Bottle of 30 NDC 65862-309-30
Bottle of 100 NDC 65862-309-01
Bottle of 1,000 NDC 65862-309-99
Store at 20° to 25°C (68° to 77°F); excursions permitted to 15° to 30°C (59° to 86°F) [see USP Controlled Room Temperature]. Protect from moisture by keeping bottle tightly closed.

Distributed by:
Aurobindo Pharma USA, Inc.
279 Princeton-Hightstown Road
East Windsor, NJ 08520

Manufactured by:
Aurobindo Pharma Limited
Hyderabad-500 032, India
Revised: 01/2022

PACKAGE LABEL-PRINCIPAL DISPLAY PANEL - 10 mg/12.5 mg (100 Tablet Bottle)

NDC 65862-308-01
Rx only
Fosinopril Sodium and
Hydrochlorothiazide
Tablets, USP
10 mg/12.5 mg
AUROBINDO 100 Tablets

PACKAGE LABEL-PRINCIPAL DISPLAY PANEL - 20 mg/12.5 mg (100 Tablet Bottle)

NDC 65862-309-01
Rx only
Fosinopril Sodium and
Hydrochlorothiazide
Tablets, USP
20 mg/12.5 mg
AUROBINDO 100 Tablets